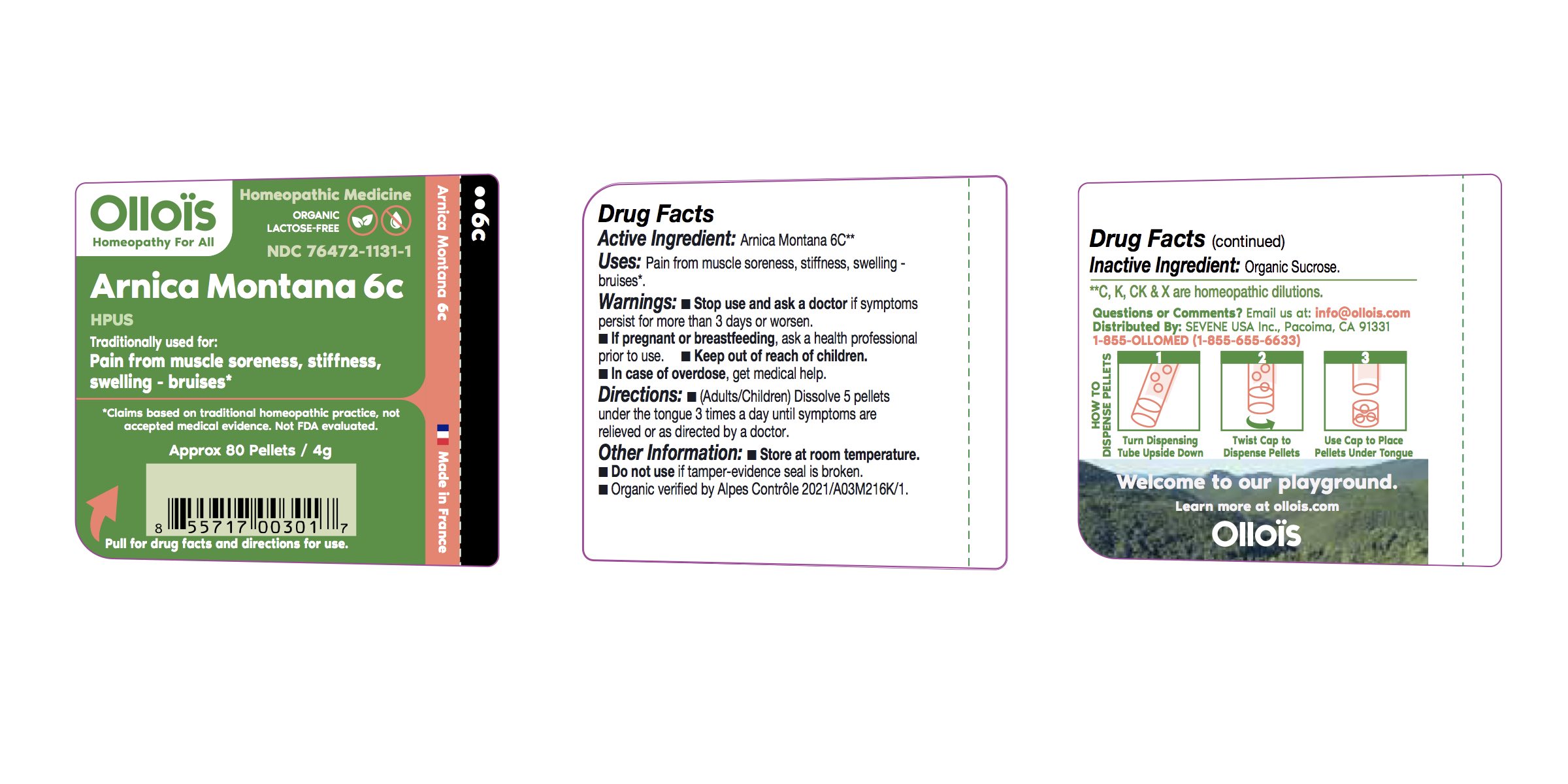 DRUG LABEL: Arnica 6c
NDC: 76472-1131 | Form: PELLET
Manufacturer: SEVENE USA
Category: homeopathic | Type: HUMAN OTC DRUG LABEL
Date: 20250211

ACTIVE INGREDIENTS: ARNICA MONTANA 6 [hp_C]/1 1
INACTIVE INGREDIENTS: SUCROSE

Sevene USA (as PLD) - ARNICA MONTANA 6C (76472-1131)

ACTIVE INGREDIENT

HOMEOPATHIC DILUTION OF HPUS ARNICA MONTANA 6c

PURPOSE

Pain from muscle soreness, stiffness, swelling - Bruises*

DIRECTIONS

(adults/children) Dissolve 5 pellets under the tongue 3 times a day until symptoms are relieved or as directed by a physician.

USE:

Condition listed above or as directed by a physician.

WARNINGS:

Stop use and ask a physician if symptoms persist for more than 3 days or worsen.

PREGNANCY OR BREAST FEEDING

If pregnant or breast-feeding, ask a health professional before use.

Keep out of reach of children.

OTHER INFORMATION:

Store at room temperature.

Do not use if pellet-dispenser seal is broken.

INACTIVE INGREDIENT:

Sucrose.

QUESTIONS?

info@ollois.com * www.ollois.com * Made in France. Not reviewed by the FDA and not guaranteed to be effective. This Homeopathic dilution may not be susceptible to scientific measurement.

USE:

Condition listed above or as directed by a physician.